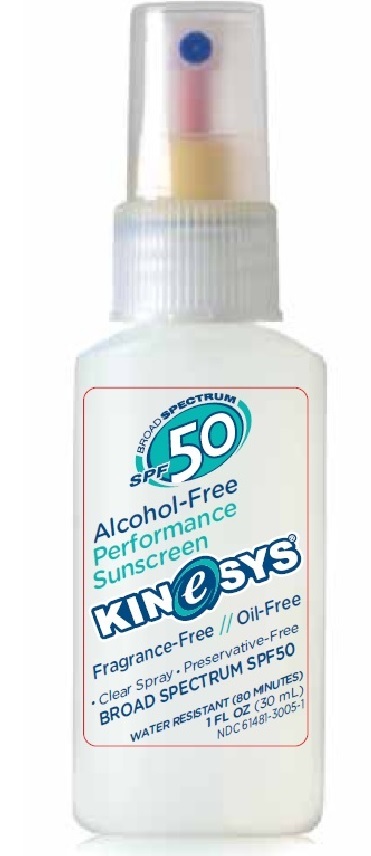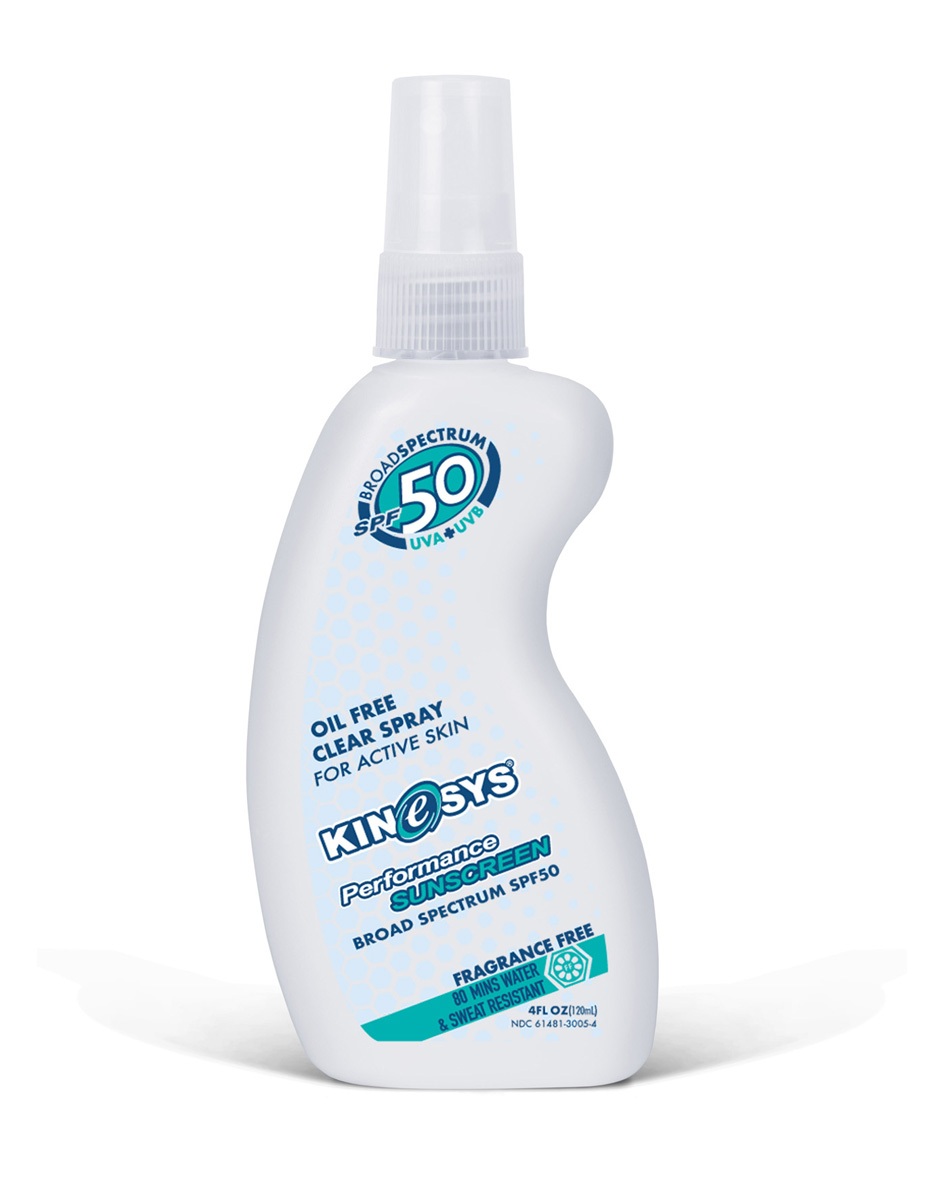 DRUG LABEL: Kinesys Broad Spectrum SPF 50 Alcohol Free Sunscreen
NDC: 61481-3005 | Form: SPRAY
Manufacturer: Wilc Healthcare Inc
Category: otc | Type: HUMAN OTC DRUG LABEL
Date: 20251013

ACTIVE INGREDIENTS: OCTOCRYLENE 100 mg/1 mL; OCTINOXATE 75 mg/1 mL; HOMOSALATE 75 mg/1 mL; OCTISALATE 50 mg/1 mL; AVOBENZONE 30 mg/1 mL
INACTIVE INGREDIENTS: CYCLOMETHICONE 5; BUTYLOCTYL SALICYLATE; ETHYLHEXYL METHOXYCRYLENE; DIPHENYLSILOXY PHENYL TRIMETHICONE; VINYLPYRROLIDONE/HEXADECENE COPOLYMER; OCTYLDODECANOL; TOCOPHEROL; LEVOMENOL

Kinesys®Broad Spectrum SPF 50 Alcohol Free Sunscreen Spray

Active Ingredients

Avobenzone 3.00% w/w
Homosalate 7.50% w/w
Octinoxate 7.50 % w/w
Octisalate 5.00% w/w
Octocrylene 10.00% w/w

Purpose

Sunscreen

Uses

- helps prevent sunburn
- if used as directed with other sun protection measures (see Directions), decreases the risk of skin cancer and early skin aging caused by the sun

Warnings

For external use only

Do not use

- on damaged or broken skin
- near flame or while smoking

When using this product

- keep out of eyes. Rinse with water to remove.

Stop use and ask a doctor

- if rash occurs

Keep out of reach of children.

If product is swallowed, get medical help or contact a Poison Control Center right away.

Directions

- Hold container 4 to 6 inches from the skin to apply
- Apply generously and spread evenly by hand 15 minutes before sun exposure
- Reapply:
  - after 80 minutes of swimming or sweating
  - immediately after towel drying
  - at least every 2 hours

- Do not spray directly onto the face. Spray into hands, and apply to the face.
- Do not apply in windy condition
- Use in well-ventilated area
- Sun Protection Measures.Spending time in the sun increases your risk of skin cancer and early skin aging. To decrease this risk, regularly use a sunscreen with a broad spectrum SPF of 15 or higher and other sun protection measures including:
  limit time in the sun, especially from 10 a.m. – 2 p.m.
  wear long-sleeve shirts, pants, hats, and sunglasses

- Children under 6 months: Ask a doctor

Inactive Ingredients

Bisabolol, Butyloctyl Salicylate, Cyclopentasiloxane, Diphenylsiloxy Phenyl Trimethicone, Octyldodecanol, Tocopherols, VP/Hexadecene Copolymer.

Other Information

- protect this product from excessive heat and direct sun

Questions or Comments?

1-888-KINeSYS [546.3797] www.kinesysactive.com